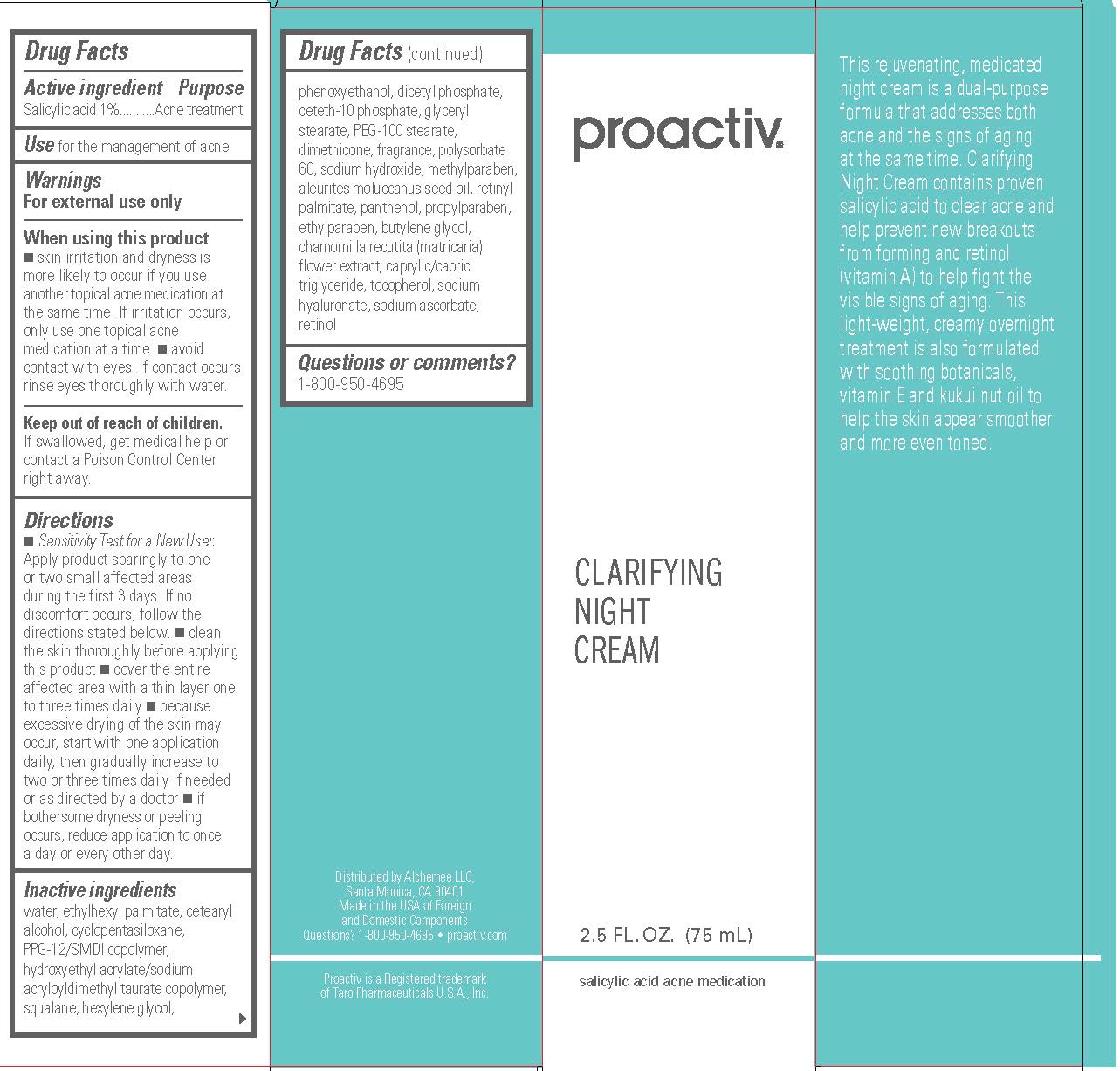 DRUG LABEL: Proactiv Clarifying Night
NDC: 11410-030 | Form: CREAM
Manufacturer: Alchemee, LLC
Category: otc | Type: HUMAN OTC DRUG LABEL
Date: 20260107

ACTIVE INGREDIENTS: SALICYLIC ACID 1 mg/100 mL
INACTIVE INGREDIENTS: WATER; ETHYLHEXYL PALMITATE; CETOSTEARYL ALCOHOL; PPG-12/SMDI COPOLYMER; CYCLOMETHICONE 5; SQUALANE; HEXYLENE GLYCOL; DIHEXADECYL PHOSPHATE; CETETH-10 PHOSPHATE; CHAMOMILE; KUKUI NUT OIL; VITAMIN A PALMITATE; PANTHENOL; GLYCERYL MONOSTEARATE; HYALURONATE SODIUM; DIMETHICONE; TOCOPHEROL; RETINOL; MEDIUM-CHAIN TRIGLYCERIDES; SODIUM ASCORBATE; BUTYLENE GLYCOL; SODIUM HYDROXIDE; POLYSORBATE 60; PHENOXYETHANOL; METHYLPARABEN; ETHYLPARABEN; PROPYLPARABEN; PEG-100 STEARATE; HYDROXYETHYL ACRYLATE/SODIUM ACRYLOYLDIMETHYL TAURATE COPOLYMER (100000 MPA.S AT 1.5%)

Proactiv Clarifying Night Cream

Drug Facts

Active ingredient

Salicylic Acid 1%

Purpose

Acne treatment

Use

for the management of acne

Warnings

For external use only

When using this product

- skin irritation and dryness is more likely to occur if you use another topical acne medication at the same time. If irritation occurs, only use one topical acne medication at a time.
- avoid contact with eyes. If contact occurs, rinse eyes thoroughly with water.

Keep out of reach of children.

If swallowed, get medical help or contact a Poison Control Center right away.

Directions

- Sensitivity Test for a New User. Apply product sparingly to one or two small affected areas during the first 3 days. If no discomfort occurs, follow the directions stated below.
- clean the skin thoroughly before applying this product
- cover the entire affected area with a thin layer one to three times daily
- because excessive drying of the skin may occur, start with one application daily, then gradually increase to two or three times daily if needed or as directed by a doctor
- if bothersome dryness or peeling occurs, reduce application to once a day or every other day.

Inactive ingredients

water, ethylhexyl palmitate, cetearyl alcohol, cyclopentasiloxane, PPG-12/SMDI copolymer, hydroxyethyl acrylate/sodium acryloyldimethyl taurate copolymer, squalane, hexylene glycol, phenoxyethanol, dicetyl phosphate, ceteth-10 phosphate, glyceryl stearate, PEG-100 stearate, dimethicone, fragrance, polysorbate 60, sodium hydroxide, methylparaben, aleurites moluccanus seed oil, retinyl palmitate, panthenol, propylparaben, ethylparaben, butylene glycol, chamomilla recutita (matricaria) flower extract, caprylic/capric triglyceride, tocopherol, sodium hyaluronate, sodium ascorbate, retinol

Questions or comments?

1-800-950-4695

Distributed by Alchemee LLC,
Santa Monica, CA 90401
Made in the USA of Foreign
and Domestic Components
Questions? 1-800-950-4695 • proactiv.com
Proactiv is a Registered trademark
of Taro Pharmaceuticals U.S.A., Inc.

PRINCIPAL DISPLAY PANEL - 2.5 FL. OZ. (75 mL)

proactiv®

CLARIFYING
NIGHT
CREAM

2.5 FL. OZ. (75 mL)

salicylic acid acne medication